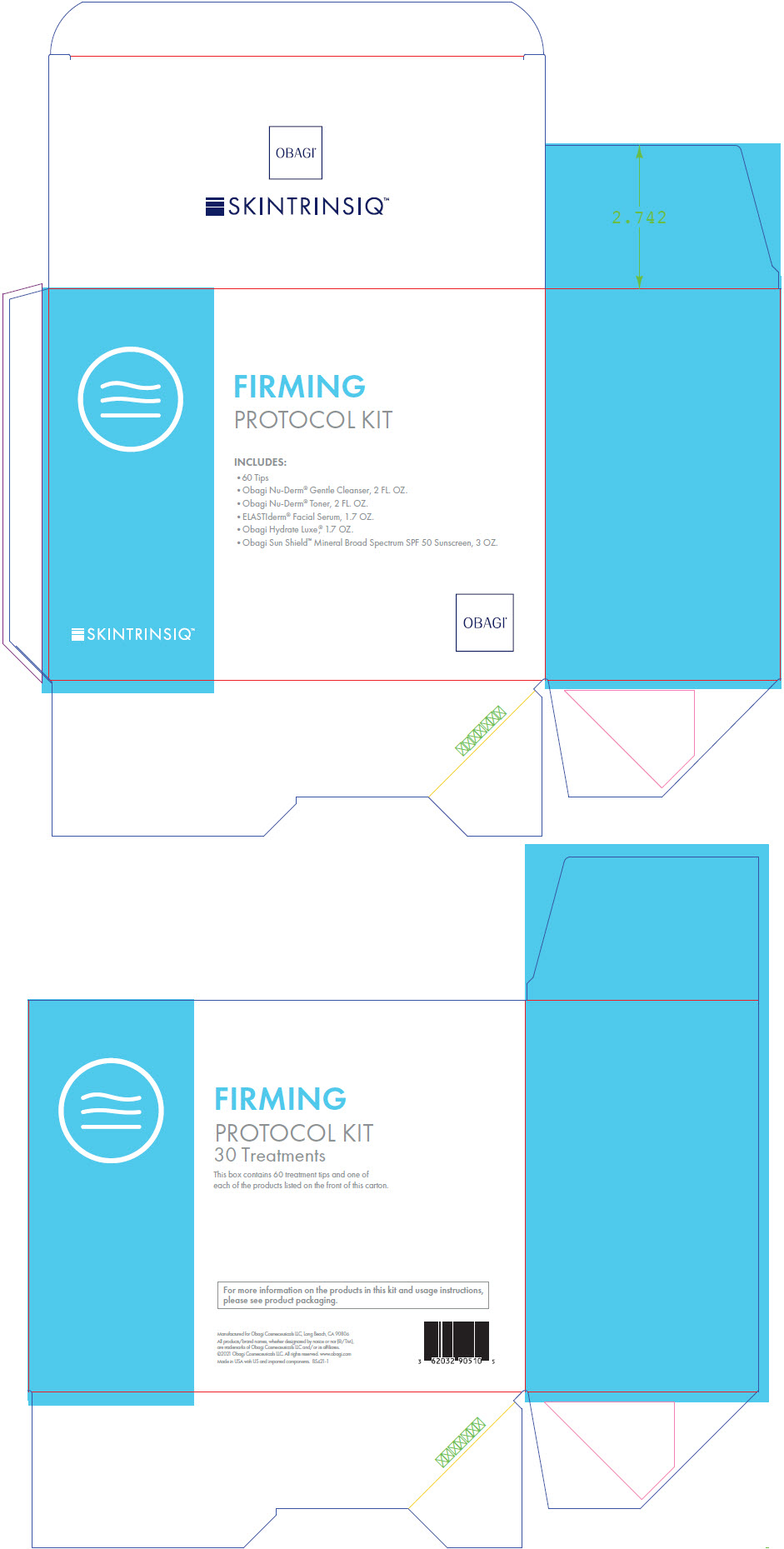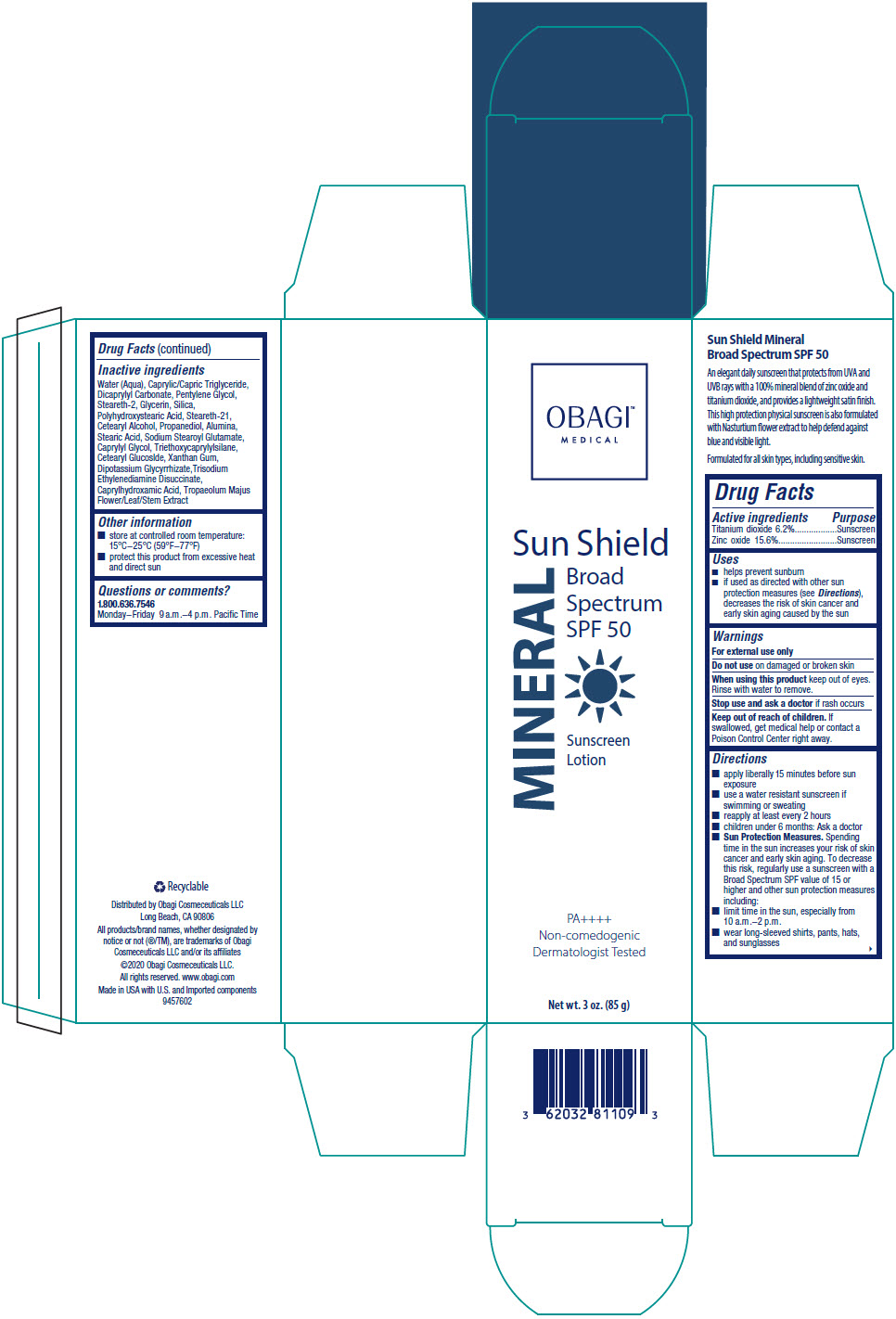 DRUG LABEL: Obagi Skintrinsiq Firming Protocol
NDC: 62032-910 | Form: KIT | Route: TOPICAL
Manufacturer: Obagi Cosmeceuticals LLC
Category: otc | Type: HUMAN OTC DRUG LABEL
Date: 20250321

ACTIVE INGREDIENTS: TITANIUM DIOXIDE 6.2 g/100 g; ZINC OXIDE 15.6 g/100 g
INACTIVE INGREDIENTS: ALUMINUM OXIDE; CAPRYLHYDROXAMIC ACID; CAPRYLYL GLYCOL; CETEARYL GLUCOSIDE; CETOSTEARYL ALCOHOL; DICAPRYLYL CARBONATE; GLYCERIN; GLYCYRRHIZINATE DIPOTASSIUM; MEDIUM-CHAIN TRIGLYCERIDES; PENTYLENE GLYCOL; POLYHYDROXYSTEARIC ACID (2300 MW); PROPANEDIOL; SILICON DIOXIDE; SODIUM STEAROYL GLUTAMATE; STEARETH-2; STEARETH-21; STEARIC ACID; TRIETHOXYCAPRYLYLSILANE; TRISODIUM ETHYLENEDIAMINE DISUCCINATE; TROPAEOLUM MAJUS FLOWERING TOP; WATER; XANTHAN GUM

Obagi ® Skintrinsiq Firming Protocol Kit

Obagi® Sun Shield Mineral Broad Spectrum SPF 50 Sunscreen

Drug Facts

ACTIVE INGREDIENT

Active ingredients | Purpose
Titanium dioxide 6.2% | Sunscreen
Zinc oxide 15.6% | Sunscreen

Uses

- helps prevent sunburn
- if used as directed with other sun protection measures (see Directions), decreases the risk of skin cancer and early skin aging caused by the sun

Warnings

For external use only

Do not use on damaged or broken skin

When using this product keep out of eyes. Rinse with water to remove.

Stop use and ask a doctor if rash occurs

Keep out of reach of children. If swallowed, get medical help or contact a Poison Control Center right away.

Directions

- apply liberally 15 minutes before sun exposure
- use a water resistant sunscreen if swimming or sweating
- reapply at least every 2 hours
- children under 6 months: Ask a doctor
- Sun Protection Measures. Spending time in the sun increases your risk of skin cancer and early skin aging. To decrease this risk, regularly use a sunscreen with a Broad Spectrum SPF value of 15 or higher and other sun protection measures including:
  - limit time in the sun, especially from 10 a.m.–2 p.m.
  - wear long-sleeved shirts, pants, hats, and sunglasses

Inactive ingredients

Water (Aqua), Caprylic/Capric Triglyceride, Dicaprylyl Carbonate, Pentylene Glycol, Steareth-2, Glycerin, Silica, Polyhydroxystearic Acid, Steareth-21, Cetearyl Alcohol, Propanediol, Alumina, Stearic Acid, Sodium Stearoyl Glutamate, Caprylyl Glycol, Triethoxycaprylylsilane, Cetearyl Glucoslde, Xanthan Gum, Dipotassium Glycyrrhizate,Trisodium Ethylenediamine Disuccinate, Caprylhydroxamic Acid, Tropaeolum Majus Flower/Leaf/Stem Extract

Other information

- store at controlled room temperature: 15°C–25°C (59°F–77°F)
- protect this product from excessive heat and direct sun

Questions or comments?

1.800.636.7546

Monday–Friday 9 a.m.–4 p.m. Pacific Time

Distributed by Obagi Cosmeceuticals LLC
Long Beach, CA 90806

PRINCIPAL DISPLAY PANEL - Kit Carton

SKINTRINSIQ™

FIRMING
PROTOCOL KIT

INCLUDES:

- 60 Tips
- Obagi Nu-Derm® gentle Cleanser, 2 FL. OZ.
- Obagi Nu-Derm® Toner, 2 FL. OZ.
- ELASTIderm® Facial Serum, 1.7 OZ.
- Obagi Hydrate Luxe®, 1.7 OZ.
- Obagi Sun Shield™ Mineral Broad Spectrum SPF 50 Sunscreen, 3 OZ.

OBAGI®

PRINCIPAL DISPLAY PANEL - 85 g Tube Carton

OBAGI™
MEDICAL

Sun Shield

MINERAL

Broad
Spectrum
SPF 50

Sunscreen
Lotion

PA++++
Non-comedogenic
Dermatologist Tested

Net wt. 3 oz. (85 g)